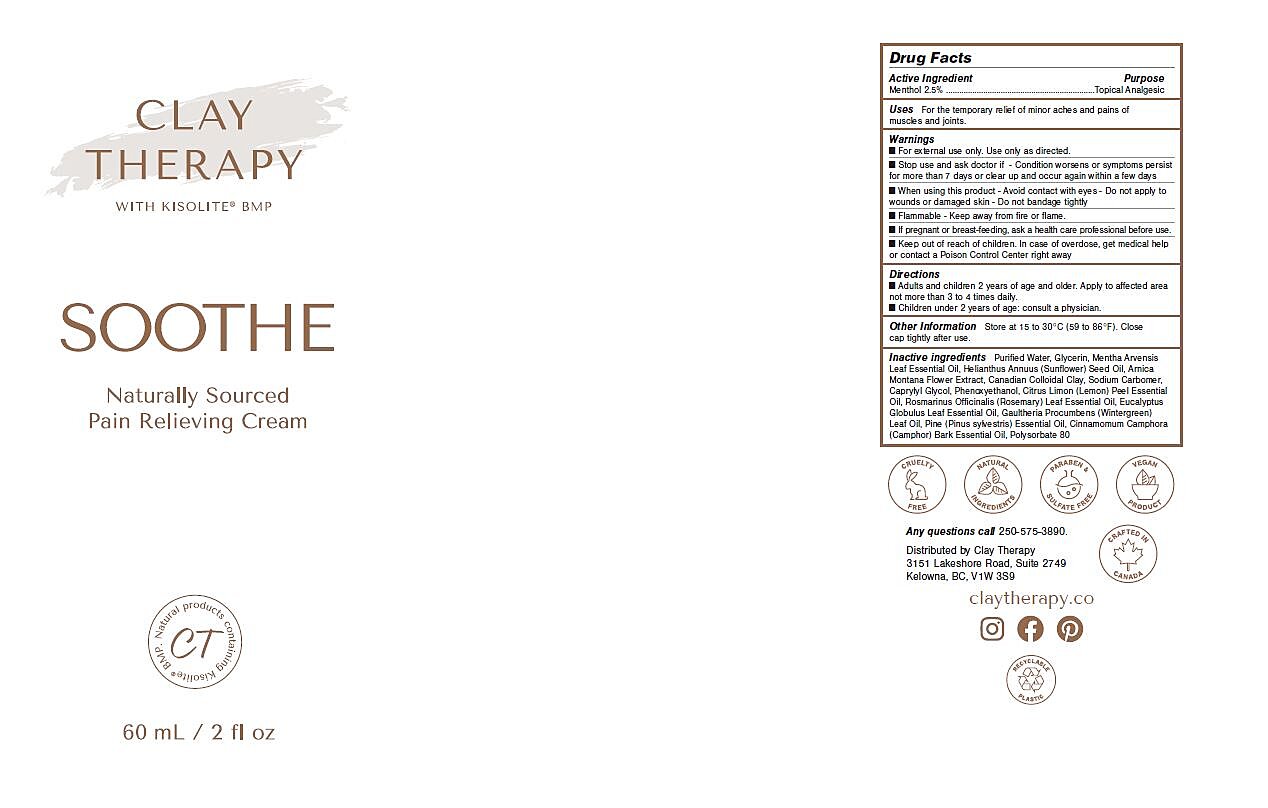 DRUG LABEL: Soothe
NDC: 81771-7001 | Form: CREAM
Manufacturer: Clay Therapy
Category: otc | Type: HUMAN OTC DRUG LABEL
Date: 20220214

ACTIVE INGREDIENTS: MENTHOL 25 mg/1 mL
INACTIVE INGREDIENTS: WATER; PINUS SYLVESTRIS WHOLE; ARNICA MONTANA FLOWER WATER; CARBOMER HOMOPOLYMER, UNSPECIFIED TYPE; CAPRYLYL GLYCOL; CITRUS LIMON FRUIT OIL; GAULTHERIA PROCUMBENS LEAF; HELIANTHUS ANNUUS SEED WAX; EUCALYPTUS GLOBULUS LEAF; PHENOXYETHANOL; CINNAMOMUM CAMPHORA LEAFY TWIG; POLYSORBATE 80; ROSMARINUS OFFICINALIS FLOWERING TOP OIL; GLYCERIN; MENTHA ARVENSIS LEAF OIL; BENTONITE

INACTIVE INGREDIENT

Purified water, Glycerin, Mentha Arvensis Leaf Essential Oil, Helianthus Annuus (Sunflower) Seed Oil, Arnica Montana Flower Extract, Canadian Colloidal Clay, Sodium Carbomer, Caprylyl Glycol, Phenoxyethanol, Citrus Limon (Lemon) Peel Essential Oil, Rosmarinus Officinalis (Rosemary) Leaf Essential Oil, Eucalyptus Globulus Leaf Essential Oil, Gaultheria Procumbens (Wintergreen) Leaf Oil, Pine (Pinus sylvestris) Essential Oil, Cinnamomum Camphora (Camphor) Bark Essential Oil, Polysorbate 80

Keep out of reach of children. In case of overdose, get medical help or contact a Poison Control Center right away

DOSAGE AND ADMINISTRATION

Adults and children 2 years of age and older. Apply to affected area not more than 3 to 4 times daily. Children under 2 years of age: consult a physician.

ACTIVE INGREDIENT

Menthol 2.5%

PURPOSE

Topical Analgesic

WARNINGS

For external use only. Use only as directed.

Stop use and ask doctor if - Condition worsens or symptoms persist for more than 7 days or clear up and occur again within a few days.

When using this product - Avoid contact with eyes - Do not apply to wounds or damaged skin - Do not bandage tightly

Flammable - Keep away from fire or flame.

If pregnant or breastfeeding, ask a health care professional before use.

Keep out of reach of children. In case of overdose, get medical help or contact a Poison Control Center right away.

INDICATIONS AND USAGE

For the temporary relief of minor aches and pains of muscles and joints.